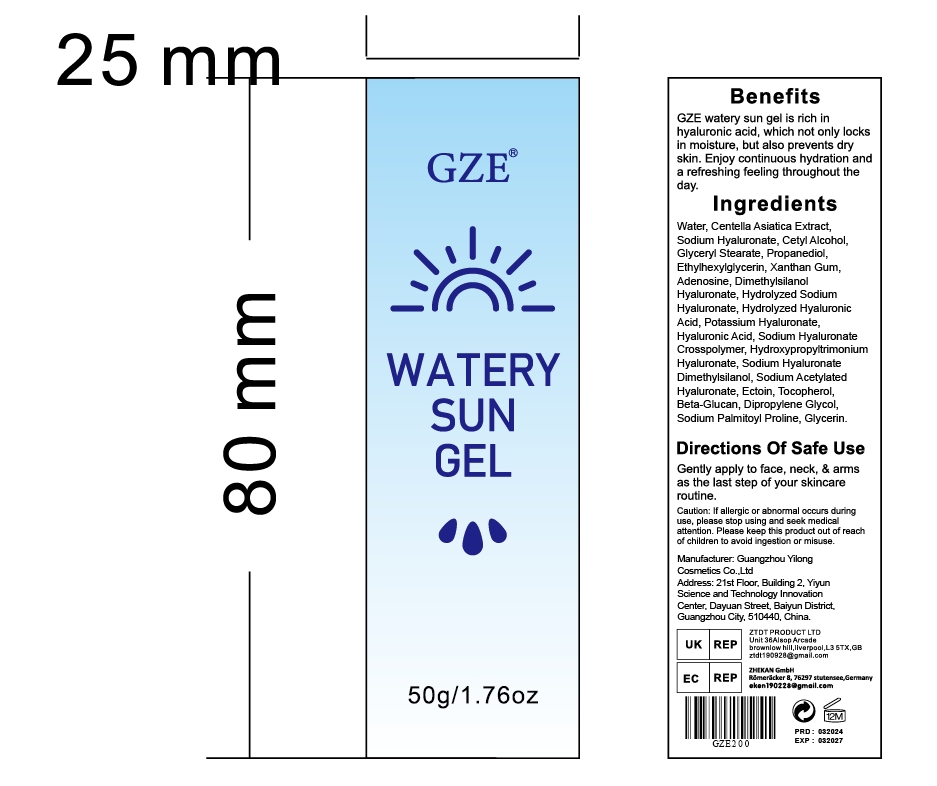 DRUG LABEL: GZE Watery Sun Gel
NDC: 83566-200 | Form: GEL
Manufacturer: Guangdong Aimu Biological Technology Co., Ltd.
Category: otc | Type: HUMAN OTC DRUG LABEL
Date: 20240514

ACTIVE INGREDIENTS: CENTELLA ASIATICA 15.17 g/120 g
INACTIVE INGREDIENTS: CETYL ALCOHOL; PROPANEDIOL; 1,3-BETA-GLUCAN SYNTHASE COMPONENT FKS1; WATER; ADENOSINE; HYALURONIC ACID; ETHYLHEXYLGLYCERIN; XANTHAN GUM; SODIUM PALMITOYL PROLINE; PEG-9 DIGLYCIDYL ETHER/SODIUM HYALURONATE CROSSPOLYMER; TOCOPHEROL; SODIUM ACETYLATED HYALURONATE; DIMETHYLSILANOL HYALURONATE; ECTOINE

GZE Watery Sun Gel

Active ingredients

WATER
TOCOPHEROL
CENTELLAASIATICA WHOLE
PEG-9 DIGLYCIDYL ETHER/SODIUM HYALURONATE CROSSPOLYMER

Purpose

Moisturising.

Uses

Gently apply to face, neck, & arms as the last step of your skincareroutine

WARNINGS

For external use only.

Stop use and ask a doctor if

rash occurs.

Do not use

on damaged or broken skin.

When using this product

keep out of eyes. Rinse with water to remove.

Keep out of reach of children.

If swallowed, get medical help or contact a Poison Control Center right away.

INACTIVE INGREDIENT

CETYLALCOHOL
SODIUM PALMITOYL PROLINE
XANTHAN GUM
PEG-9 DIGLYCIDYL ETHERISODIUM HYALURONATE CROSSPOLYMER
ETHYLHEXYLGLYCERIN
ECTOINE
DIMETHYLSILANOL HYALURONATE
CENTELLAASIATICA WHOLE
TOCOPHEROL
ADENOSINE
WATER
PROPANEDIOL
1.3-BETA-GLUCAN SYNTHASE COMPONENT FKS1